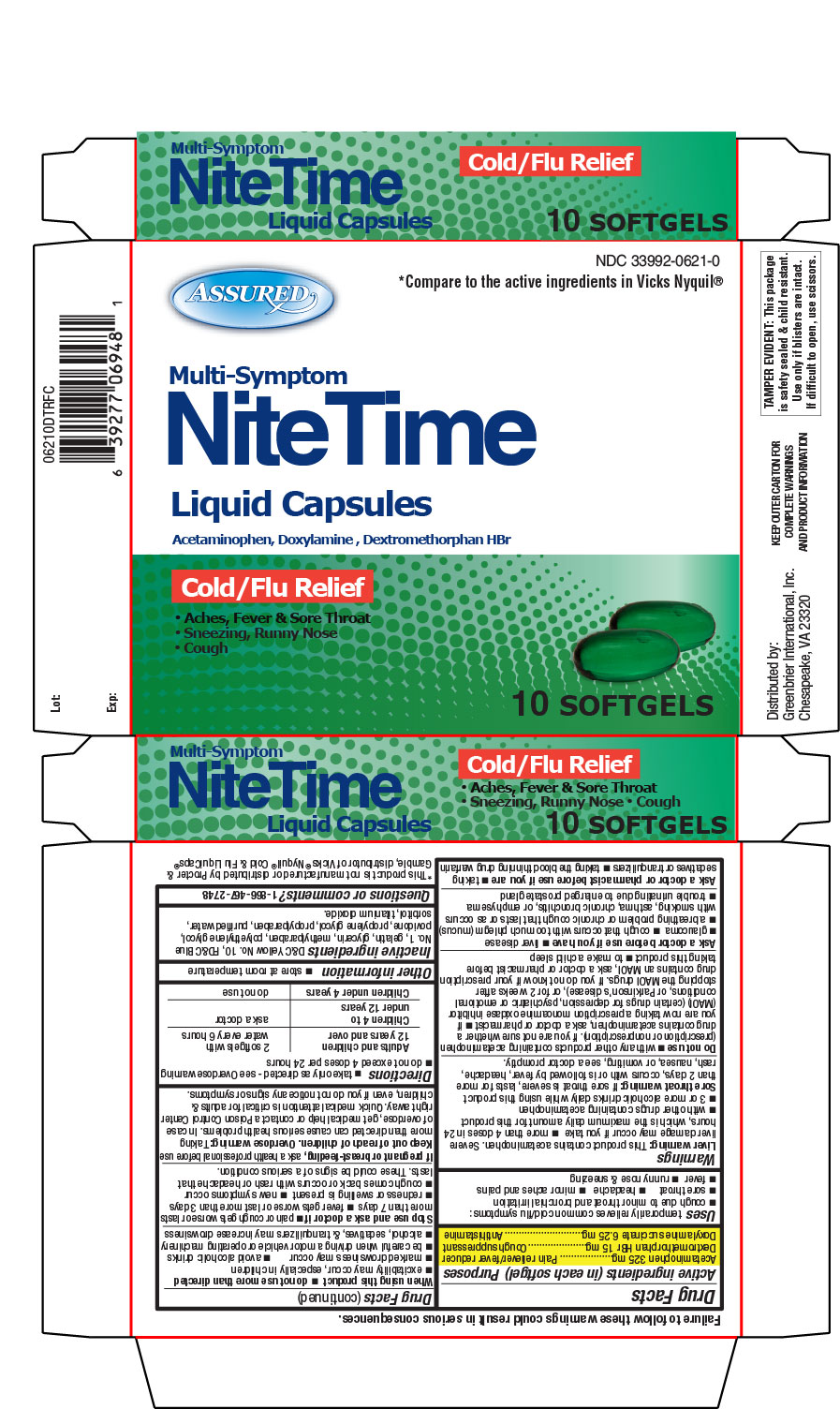 DRUG LABEL: NiteTime
NDC: 33992-0621 | Form: CAPSULE, LIQUID FILLED
Manufacturer: Greenbrier International
Category: otc | Type: HUMAN OTC DRUG LABEL
Date: 20140102

ACTIVE INGREDIENTS: Acetaminophen 325 mg/1 1; Dextromethorphan Hydrobromide 15 mg/1 1; Doxylamine Succinate 6.25 mg/1 1
INACTIVE INGREDIENTS: D&C Yellow No. 10; FD&C Blue No. 1; gelatin; glycerin; METHYLPARABEN; polyethylene glycols; POVIDONES; propylene glycol; PROPYLPARABEN; water; sorbitol; titanium dioxide

NiteTime Multi-Symptom Liquid Capsules Cold/Flu Relief

Drug Facts

Active Ingredient

Active ingredients (in each softgel)

Acetaminophen 325 mg

Dextromethorphan HBr 15 mg

Doxylamine succinate 6.25 mg

Purpose

Purpose

Pain reliever/fever reducer

Cough suppressant

Antihistamine

Uses

temporarily relieves common cold/flu symptoms

- cough due to minor throat and bronchial irritation
- sore throat
- headache
- minor aches & pains
- fever
- runny nose & sneezing

Warnings

Liver warning

This product contains acetaminophen. Severe liver damage may occur if you take

- more than 4 doses in 24 hours, which is the maximum daily amount for this product
- with other drugs containing acetaminophen
- 3 or more alcoholic drinks daily while using this product

Sore throat warning

If sore throat is severe, lasts for more than 2 days, occurs with or is followed by fever, headache, rash, nausea, or vomiting, see a doctor promptly.

Do not use

- with any other drug containing acetaminophen (prescription or nonprescription). If you are not sure whether a drug contains acetaminophen, ask a doctor or pharmacist.
- if you are now taking a prescription monoamine oxidase inhibitor (MAOI) (certain drugs for depression, psychiatric or emotional conditions, or Parkinson's disease), or for 2 weeks after stopping the MAOI drug. If you do not know if your prescription drug contains an MAOI, ask a doctor or pharmacist before taking this product.
- to make a child sleep

Ask a doctor before use if you have

- liver disease
- glaucoma
- cough that occurs with too much phlegm (mucus)
- a breathing problem or chronic cough that lasts or as occurs with smoking, asthma, chronic bronchitis or emphysema
- trouble urinating due to enlarged prostate gland

Ask a doctor or pharmacist before use if you are

- taking sedatives or tranquilizers
- taking the blood thinning drug warfarin

When using this product

- do not use more than directed
- excitability may occur, especially in children
- marked drowsiness may occur
- avoid alcoholic drinks
- be careful when driving a motor vehicle or operating machinery
- alcohol, sedatives, & tranquilizers may increase drowsiness

Stop use and ask a doctor if

- pain or cough gets worse or lasts more than 7 days
- fever gets worse or lasts more than 3 days
- redness or swelling is present
- new symptoms occur
- cough comes back or occurs with rash or headache that lasts. These could be signs of a serious condition.

PREGNANCY OR BREAST FEEDING

If pregnant or breast-feeding, ask a health professional before use.

Keep out of reach of children.

Overdose warning

Taking more than directed can cause serious health problems. In case of overdose, get medical help or contact a Poison Control Center right away. Quick medical attention is critical for adults & for children even if you do not notice any signs or symptoms.

Directions

- take only as directed - see Overdose warning
- do not exceed 4 doses per 24 hrs

Adults & children 12 years and over | 2 softgels with water every 6 hrs
Children 4 to under 12 years | ask a doctor
Children under 4 years | do not use

Other information

- store at room temperature

Inactive ingredients

D&C Yellow No. 10, FD&C Blue No. 1, gelatin, glycerin, methylparaben, polyethylene glycol, povidone, propylene glycol, propylparaben, purified water, sorbitol, titanium dioxide

Questions?

1-866-467-2748

This product is not manufactured or distributed by Procter & Gamble, distributor of Vicks® Nyquil® Cold & Flu Liquicaps®

PRINCIPAL DISPLAY PANEL - 10 Softgel Carton

Assured

Multi-Symptom

NiteTime

Acetaminophen, Doxylamine, Dextromethorphan HBr

Cold/Flu Relief

- Aches & Sore Throat
- Sneezing, Runny Nose
- Cough
  10 Softgels